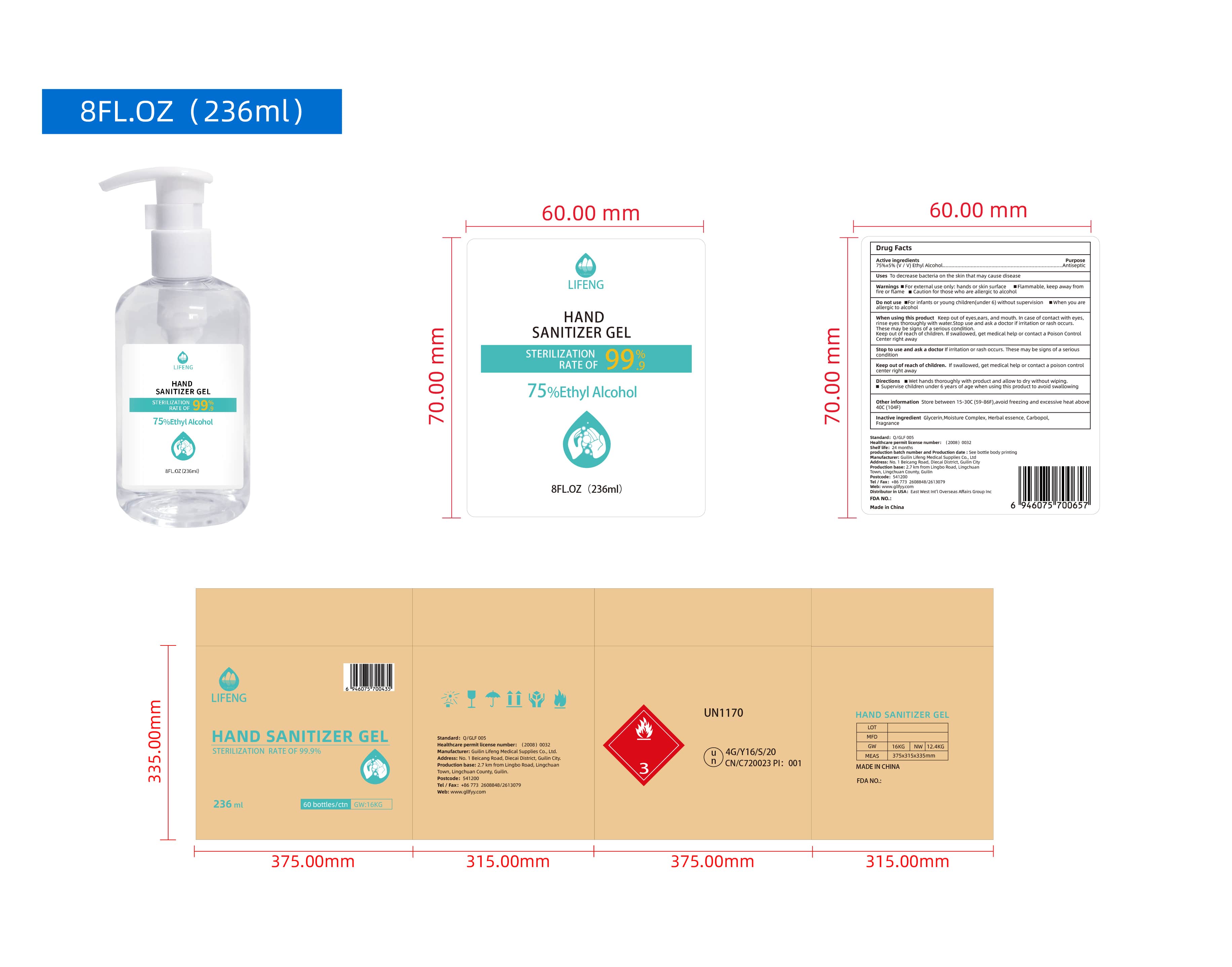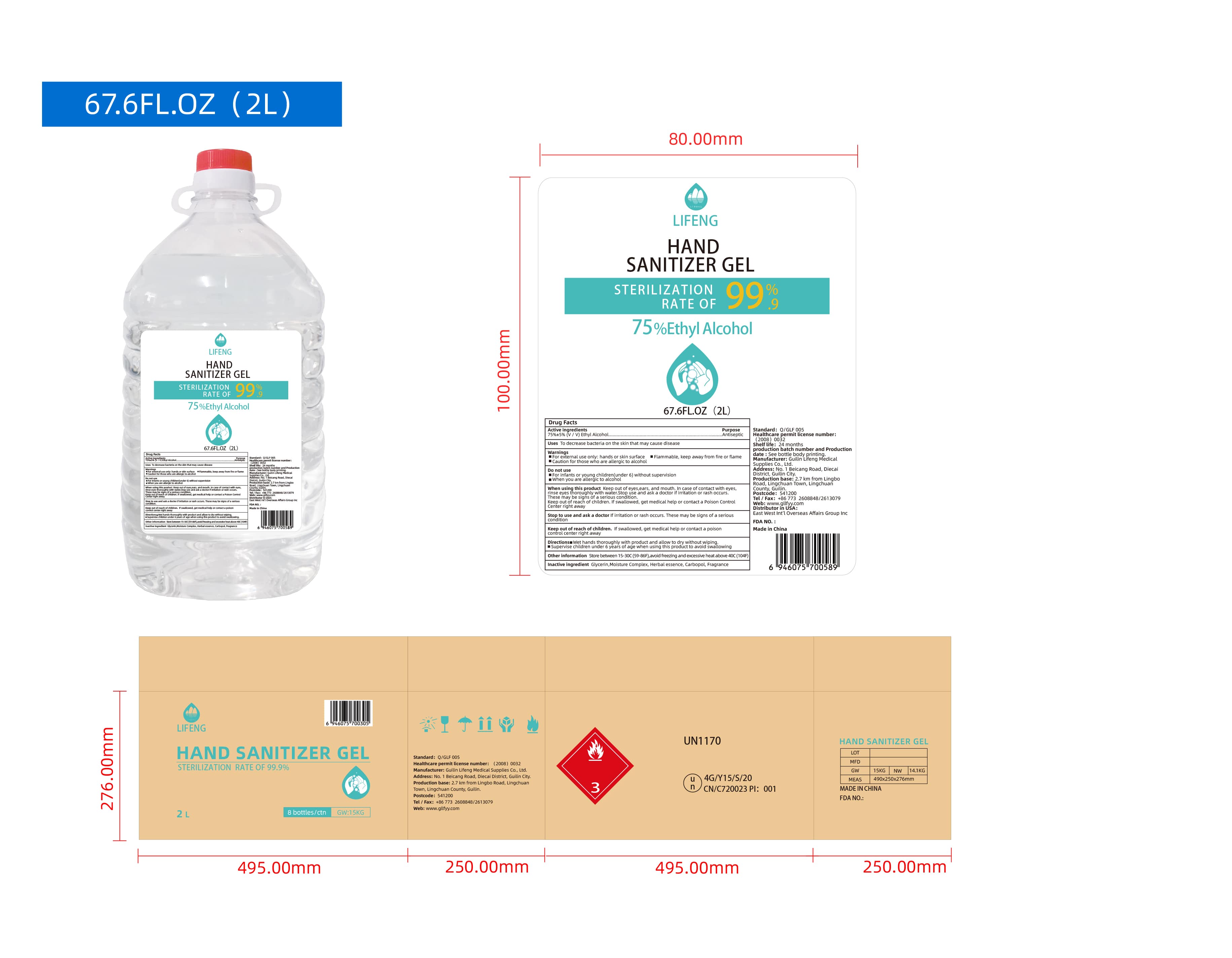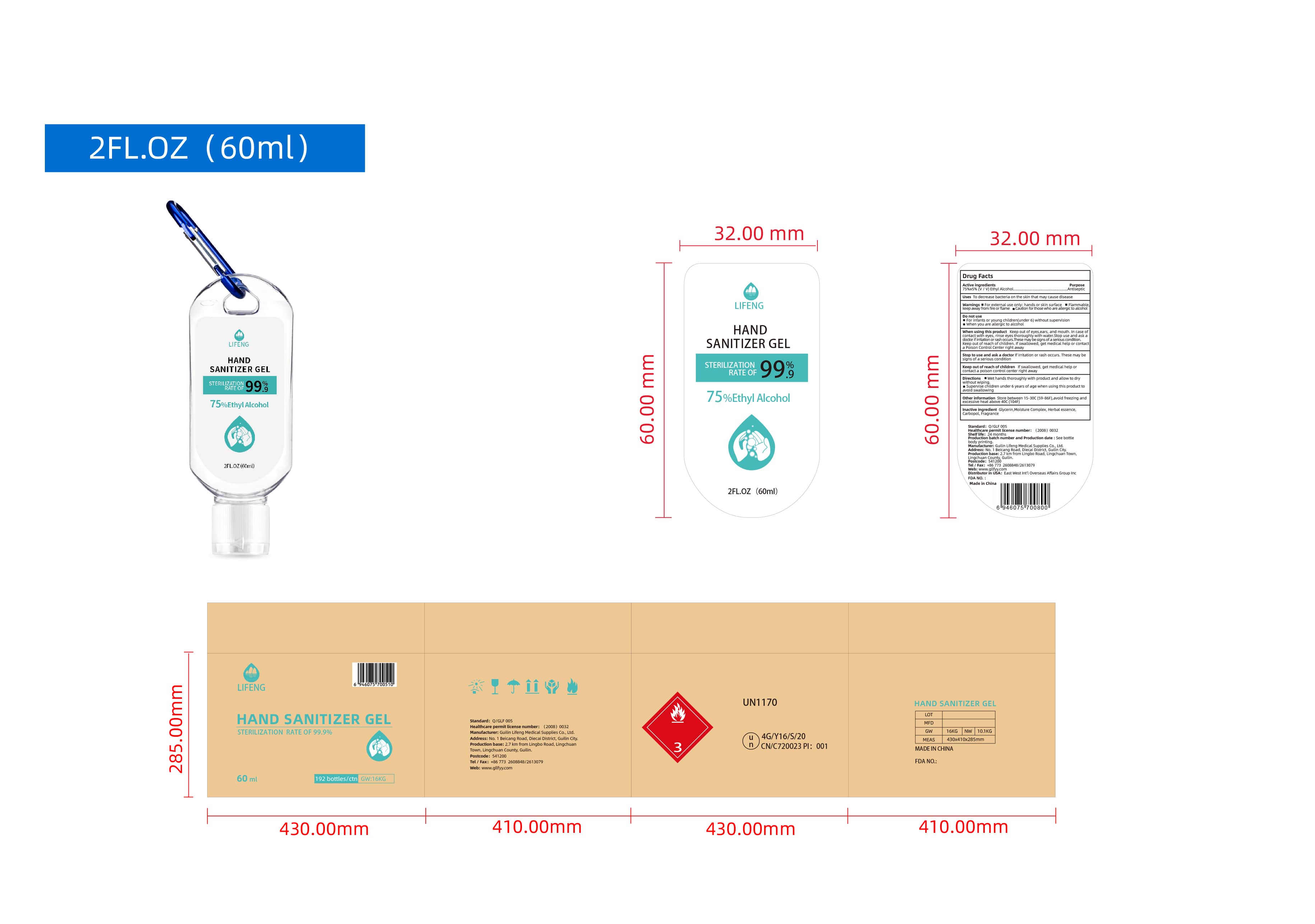 DRUG LABEL: Hand Sanitizer
NDC: 81898-103 | Form: GEL
Manufacturer: GUILIN LIFENG MEDICAL SUPPLIES CO.,LTD.
Category: otc | Type: HUMAN OTC DRUG LABEL
Date: 20210517

ACTIVE INGREDIENTS: ISOPROPYL ALCOHOL 75 mL/100 mL
INACTIVE INGREDIENTS: GLYCERIN 1.45 mL/100 mL; HYDROGEN PEROXIDE 0.125 mL/100 mL; WATER

Hand Sanitizer Gel

This is a hand sanitizer manufactured according to the Temporary Policy for Preparation of Certain Alcohol-Based Hand Sanitizer Products During the Public Health Emergency (CoViD-19); Guidance for Industry.

The hand sanitizer is manufactured using only the following United States Pharmacopoeia (USP) grade ingredients in the preparation of the product (percentage in final product formulation) consistent with World Health Organization (WHO) recommendations:

1. Ethyl Alcohol (75%, v/v) in an aqueous solution denatured according to Alcohol and Tobacco Tax and Trade Bureau regulations in 27 CFR part 20.
2. Glycerin (1.45% v/v).
3. Moisture Complex.
4. Herbal Essence (0.125% v/v).
5. Carbopol
6. Fragrance

The firm does not add other active or inactive ingredients. Different or additional ingredients may impact the quality and potency of the product.

Active Ingredient(s)

Ethyl Alcohol 75% v/v. Purpose: Antiseptic

Purpose

Antiseptic, Hand Sanitizer

Use

Hand Sanitizer to decrease bacteria on the skin that may cause disease.

Warnings

For external use only: hands or skin surface

Flammable, keep away from fire or flame

Caution for those who are allergic to alcohol

Do not use

- For infants or young children (under 6) without supervision
- When you are allergic to alcohol

When using this product keep out of eyes, ears, and mouth. In case of contact with eyes, rinse eyes thoroughly with water.
Stop use and ask a doctor if irritation or rash occurs. These may be signs of a serious condition.
Keep out of reach of children. If swallowed, get medical help or contact a Poison Control Center right away.

Stop use and ask a doctor if irritation or rash occurs. These may be signs of a serious condition.

Keep out of reach of children. If swallowed, get medical help or contact a Poison Control Center right away.

Directions

- Wet hands thoroughly with product and allow to dry withuot wiping.
- Supervise children under 6 years of age when using this product to avoid swallowing.

Other information

- Store between 15-30C (59-86F)
- Avoid freezing and excessive heat above 40C (104F)

Inactive ingredients

Glycerin, Moisture Complex, Herbal Essence, Carbopol, Fragrance